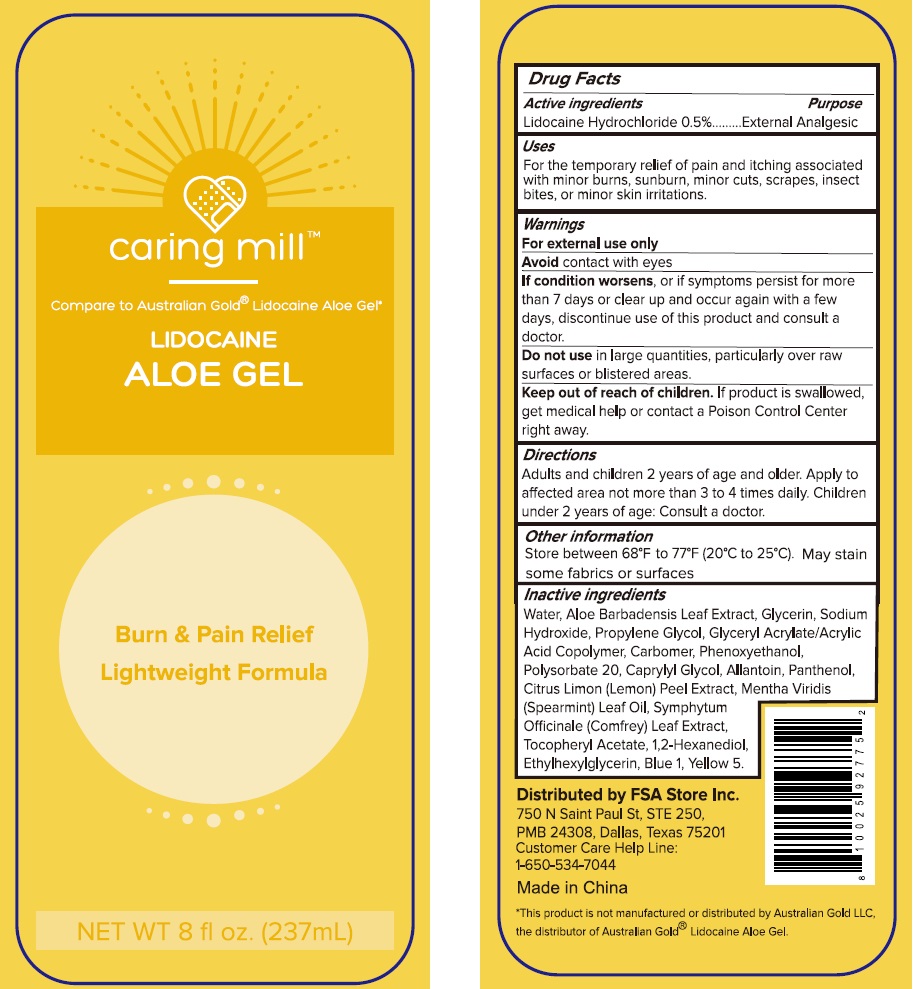 DRUG LABEL: Caring mill Lidocaine Aloe Gel Burn and Pain Relief
NDC: 81522-953 | Form: LIQUID
Manufacturer: FSA Store Inc.
Category: otc | Type: HUMAN OTC DRUG LABEL
Date: 20240112

ACTIVE INGREDIENTS: LIDOCAINE HYDROCHLORIDE 5 mg/1 mL
INACTIVE INGREDIENTS: WATER; ALOE VERA LEAF; GLYCERIN; SODIUM HYDROXIDE; PROPYLENE GLYCOL; CARBOMER HOMOPOLYMER, UNSPECIFIED TYPE; PHENOXYETHANOL; POLYSORBATE 20; CAPRYLYL GLYCOL; ALLANTOIN; PANTHENOL; LEMON PEEL; SPEARMINT OIL; SYMPHYTUM X UPLANDICUM LEAF; .ALPHA.-TOCOPHEROL ACETATE; 1,2-HEXANEDIOL; ETHYLHEXYLGLYCERIN; FD&C BLUE NO. 1; FD&C YELLOW NO. 5

Caring mill Lidocaine Aloe Gel Burn and Pain Relief

Active ingredients

Lidocaine Hydrochloride 0.5%

Purpose

External Analgesic

Uses

For the temporary relief of pain and itching associated with minor burns, sunburn, minor cuts, scrapes, insect bites, or minor skin irritations.

Warnings

For external use only
Avoidcontact with eyes
If condition worsens, or if symptoms persist for more than 7 days or clear up and occur again with a few days, discontinue use of this product and consult a doctor.

Do not use

in large quantities, particularly over raw surfaces or blistered areas.

Keep out of reach of children.

If product is swallowed, get medical help or contact a Poison Control Center right away.

Directions

Adults and children 2 years of age and older. Apply to affected area not more than 3 to 4 times daily. Children under 2 years of age: Consult a doctor.

Other information

Store between 68°F to 77°F (20°C to 25°). May stain some fabrics or surfaces

Inactive ingredients

Water, Aloe Barbadensis Leaf Extract, Glycerin, Sodium Hydroxide, Propylene Glycol, Glyceryl Acrylate/Acrylic Acid Copolymer, Carbomer, Phenoxyethanol, Polysorbate 20, Caprylyl Glycol, Allantoin, Panthenol, Citrus Limon (Lemon) Peel Extract, Mentha Viridis (Spearmint) Leaf Oil, Symphytum Officinale (Comfrey) Leaf Extract, Tocopheryl Acetate, 1,2-Hexanediol, Ethylhexylglycerin, Blue 1, Yellow 5.